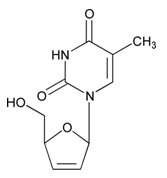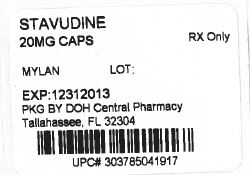 DRUG LABEL: Stavudine
NDC: 53808-0852 | Form: CAPSULE
Manufacturer: State of Florida DOH Central Pharmacy
Category: prescription | Type: HUMAN PRESCRIPTION DRUG LABEL
Date: 20130930

ACTIVE INGREDIENTS: STAVUDINE 20 mg/1 1
INACTIVE INGREDIENTS: ANHYDROUS LACTOSE; MAGNESIUM STEARATE; CELLULOSE, MICROCRYSTALLINE; SODIUM STARCH GLYCOLATE TYPE A POTATO; D&C RED NO. 28; FD&C BLUE NO. 1; FD&C RED NO. 40; GELATIN; TITANIUM DIOXIDE; FERROSOFERRIC OXIDE; POTASSIUM HYDROXIDE; PROPYLENE GLYCOL; SHELLAC

HIGHLIGHTS OF PRESCRIBING INFORMATION

These highlights do not include all the information needed to use stavudine safely and effectively. See full prescribing information for stavudine capsules.
Stavudine Capsules, USP
Initial U.S. Approval: 1994

RECENT MAJOR CHANGES

Dosage and Administration: Dosage Adjustment
(Peripheral Neuropathy) (2.3) – removal 12/2010

Warnings and Precautions
Fat Redistribution (5.5) 12/2010
Immune Reconstitution Syndrome (5.6) 11/2011

WARNING: LACTIC ACIDOSIS and HEPATOMEGALY with STEATOSIS; PANCREATITIS

See full prescribing information for complete boxed warning

- Lactic acidosis and severe hepatomegaly with steatosis, including fatal cases. Fatal lactic acidosis has been reported in pregnant women who received the combination of stavudine and didanosine. (5.1)
- Fatal and nonfatal pancreatitis have occurred when stavudine was part of a combination regimen that included didanosine. (5.4)

1 INDICATIONS AND USAGE

Stavudine is a nucleoside reverse transcriptase inhibitor for use in combination with other antiretroviral agents for the treatment of human immunodeficiency virus (HIV)-1 infection. (1)

2 DOSAGE AND ADMINISTRATION

- Recommended dosage for adults:
  - less than 60 kg: 30 mg every 12 hours (2.1)
  - at least 60 kg: 40 mg every 12 hours (2.1)
- Recommended dosage for pediatric patients:
  - newborns from birth to 13 days old: 0.5 mg/kg every 12 hours (2.2)
  - at least 14 days old and weighing less than 30 kg: 1 mg/kg every 12 hours (2.2)
  - weighing at least 30 kg: adult dose (2.2)
- Renal impairment: Dose adjustment is recommended for CrCl ≤ 50 mL/min. (2.3)

3 DOSAGE FORMS AND STRENGTHS

- Capsules: 15 mg, 20 mg, 30 mg, 40 mg (3, 16.1)

4 CONTRAINDICATIONS

Stavudine capsules are contraindicated in patients with clinically significant hypersensitivity to stavudine or to any of the components of this product. (4)

WARNINGS AND PRECAUTIONS

- Lactic acidosis/severe hepatomegaly with steatosis: Suspend treatment with stavudine in patients who develop clinical symptoms or signs with or without laboratory findings. (5.1)
- Hepatic toxicity: May be severe, fatal. Consider interruption or discontinuation. Avoid use in combination with didanosine and hydroxyurea. Risk of hepatic decompensation exists when used in combination with interferon and ribavirin; closely monitor and consider discontinuation of stavudine. (5.2)
- Neurologic symptoms: Motor weakness, most often seen in the setting of lactic acidosis, may mimic Guillain-Barré syndrome; discontinue treatment. Monitor for peripheral neuropathy, which can be severe; treatment discontinuation should be considered. (5.3)
- Pancreatitis: Suspend treatment, resume with particular caution and close monitoring and avoid use in combination with didanosine. (5.4)
- Patients may develop redistribution/accumulation of body fat, monitor for signs and symptoms of lipoatrophy/lipodystrophy. Alternative antiretrovirals should be considered. (5.5)
- Patients may develop immune reconstitution syndrome. (5.6)

6 ADVERSE REACTIONS

- In adults, the most common adverse reactions are headache, diarrhea, neuropathy, rash, nausea and vomiting. (6.1)
- Adverse reactions in pediatric patients were consistent with those seen in adults. (6.2)

To report SUSPECTED ADVERSE REACTIONS, contact Mylan Pharmaceuticals Inc. at 1-877-446-3679 (1-877-4-INFO-RX) or FDA at 1-800-FDA-1088 or www.fda.gov/medwatch.

7 DRUG INTERACTIONS

- Coadministration of stavudine with zidovudine should be avoided. (7)
- Coadministration of stavudine and doxorubicin or ribavirin should be undertaken with caution. (7)

USE IN SPECIFIC POPULATIONS

- Pregnancy: Fatal lactic acidosis has been reported in pregnant women who received both didanosine and stavudine with other agents. This combination should be used with caution during pregnancy and only if the potential benefit clearly outweighs the potential risk to the fetus. Pregnancy registry available. (8.1)
- Nursing mothers should be instructed not to breast-feed due to the potential for postnatal HIV transmission. (8.3)

FULL PRESCRIBING INFORMATION

WARNING: LACTIC ACIDOSIS and HEPATOMEGALY with STEATOSIS; PANCREATITIS

Lactic acidosis and severe hepatomegaly with steatosis, including fatal cases, have been reported with the use of nucleoside analogues alone or in combination, including stavudine and other antiretrovirals. Fatal lactic acidosis has been reported in pregnant women who received the combination of stavudine and didanosine with other antiretroviral agents. The combination of stavudine and didanosine should be used with caution during pregnancy and is recommended only if the potential benefit clearly outweighs the potential risk [see Warnings and Precautions (5.1)].

Fatal and nonfatal pancreatitis have occurred during therapy when stavudine was part of a combination regimen that included didanosine in both treatment-naive and treatment-experienced patients, regardless of degree of immunosuppression [see Warnings and Precautions (5.4)].

1 INDICATIONS AND USAGE

Stavudine capsules, in combination with other antiretroviral agents, are indicated for the treatment of human immunodeficiency virus (HIV)-1 infection [see Clinical Studies (14)].

2 DOSAGE AND ADMINISTRATION

The interval between doses of stavudine capsules should be 12 hours. Stavudine capsules may be taken with or without food.

2.1 Recommended Adult Dosage

The recommended adult dosage is based on body weight as follows:

- For patients weighing less than 60 kg: 30 mg every 12 hours.
- For patients weighing at least 60 kg: 40 mg every 12 hours.

2.2 Recommended Pediatric Dosage

- For newborns from birth to 13 days old: 0.5 mg/kg given every 12 hours.
- For pediatric patients at least 14 days old and weighing less than 30 kg: 1 mg/kg given every 12 hours.
- For pediatric patients weighing at least 30 kg: use the recommended adult dosage.

Adult Patients

Stavudine capsules may be administered to adult patients with impaired renal function with an adjustment in dosage as shown in Table 1.

Table 1: Recommended Dosage Adjustment for Adult Patients with Renal Impairment
Creatinine Clearance; (mL/min) | Recommended Stavudine Dose by Patient Weight
Creatinine Clearance; (mL/min) | at least 60 kg | less than 60 kg
greater than 50 | 40 mg every 12 hours | 30 mg every 12 hours
26 to 50 | 20 mg every 12 hours | 15 mg every 12 hours
10 to 25 | 20 mg every 24 hours | 15 mg every 24 hours
Hemodialysis | 20 mg every 24 hours [Administered after the completion of hemodialysis on dialysis days and at the same time of day on non-dialysis days.] | 15 mg every 24 hours

Pediatric Patients

Since urinary excretion is also a major route of elimination of stavudine in pediatric patients, the clearance of stavudine may be altered in children with renal impairment. There are insufficient data to recommend a specific dose adjustment of stavudine capsules in this patient population.

3 DOSAGE FORMS AND STRENGTHS

- The 15 mg capsules have a hard-shell gelatin capsule with an off-white opaque cap and a pink opaque body filled with a white to off-white powder. The capsule is axially printed with M 154 in black ink on both the cap and body.
- The 20 mg capsules have a hard-shell gelatin capsule with a pink opaque cap and a pink opaque body filled with a white to off-white powder. The capsule is axially printed with M 155 in black ink on both the cap and body.
- The 30 mg capsules have a hard-shell gelatin capsule with an off-white opaque cap and a light orange opaque body filled with a white to off-white powder. The capsule is axially printed with M 137 in black ink on both the cap and body.
- The 40 mg capsules have a hard-shell gelatin capsule with a light orange opaque cap and a light orange opaque body filled with a white to off-white powder. The capsule is axially printed with M 138 in black ink on both the cap and body.

4 CONTRAINDICATIONS

Stavudine capsules are contraindicated in patients with clinically significant hypersensitivity to stavudine or to any of the components contained in the formulation.

WARNINGS AND PRECAUTIONS

5.1 Lactic Acidosis/Severe Hepatomegaly with Steatosis

Lactic acidosis and severe hepatomegaly with steatosis, including fatal cases, have been reported with the use of nucleoside analogues alone or in combination, including stavudine and other antiretrovirals. Although relative rates of lactic acidosis have not been assessed in prospective well controlled trials, longitudinal cohort and retrospective studies suggest that this infrequent event may be more often associated with antiretroviral combinations containing stavudine. Female gender, obesity and prolonged nucleoside exposure may be risk factors. Fatal lactic acidosis has been reported in pregnant women who received the combination of stavudine and didanosine with other antiretroviral agents. The combination of stavudine and didanosine should be used with caution during pregnancy and is recommended only if the potential benefit clearly outweighs the potential risk [see Use in Specific Populations (8.1)].

Particular caution should be exercised when administering stavudine to any patient with known risk factors for liver disease; however, cases of lactic acidosis have also been reported in patients with no known risk factors. Generalized fatigue, digestive symptoms (nausea, vomiting, abdominal pain and unexplained weight loss); respiratory symptoms (tachypnea and dyspnea); or neurologic symptoms, including motor weakness [see Warnings and Precautions (5.3)] might be indicative of the development of symptomatic hyperlactatemia or lactic acidosis syndrome.

Treatment with stavudine should be suspended in any patient who develops clinical or laboratory findings suggestive of symptomatic hyperlactatemia, lactic acidosis or pronounced hepatotoxicity (which may include hepatomegaly and steatosis even in the absence of marked transaminase elevations). Permanent discontinuation of stavudine should be considered for patients with confirmed lactic acidosis.

5.2 Hepatic Toxicity

The safety and efficacy of stavudine have not been established in HIV-infected patients with significant underlying liver disease. During combination antiretroviral therapy, patients with preexisting liver dysfunction, including chronic active hepatitis, have an increased frequency of liver function abnormalities, including severe and potentially fatal hepatic adverse events, and should be monitored according to standard practice. If there is evidence of worsening liver disease in such patients, interruption or discontinuation of treatment must be considered.

Hepatotoxicity and hepatic failure resulting in death were reported during post-marketing surveillance in HIV-infected patients treated with hydroxyurea and other antiretroviral agents. Fatal hepatic events were reported most often in patients treated with the combination of hydroxyurea, didanosine and stavudine. This combination should be avoided [see Adverse Reactions (6)].

Use with Interferon and Ribavirin-based Regimens

In vitro studies have shown ribavirin can reduce the phosphorylation of pyrimidine nucleoside analogues such as stavudine. Although no evidence of a pharmacokinetic or pharmacodynamic (e.g., loss of HIV-1/HCV virologic suppression) interaction was seen when ribavirin was coadministered with stavudine in HIV-1/HCV co-infected patients [see Drug Interactions (7)], hepatic decompensation (some fatal) has occurred in HIV-1/HCV co-infected patients receiving combination antiretroviral therapy for HIV-1 and interferon and ribavirin. Patients receiving interferon with or without ribavirin and stavudine should be closely monitored for treatment-associated toxicities, especially hepatic decompensation. Discontinuation of stavudine should be considered as medically appropriate. Dose reduction or discontinuation of interferon, ribavirin or both should also be considered if worsening clinical toxicities are observed, including hepatic decompensation (e.g., Child-Pugh > 6) (see the full prescribing information for interferon and ribavirin).

5.3 Neurologic Symptoms

Motor weakness has been reported rarely in patients receiving combination antiretroviral therapy including stavudine. Most of these cases occurred in the setting of lactic acidosis. The evolution of motor weakness may mimic the clinical presentation of Guillain-Barré syndrome (including respiratory failure). If motor weakness develops, stavudine should be discontinued. Symptoms may continue or worsen following discontinuation of therapy.

Peripheral sensory neuropathy, manifested by numbness, tingling or pain in the hands or feet, has been reported in patients receiving stavudine therapy. Peripheral neuropathy, which can be severe, is dose related and occurs more frequently in patients with advanced HIV-1 disease, a history of peripheral neuropathy, or in patients receiving other drugs that have been associated with neuropathy, including didanosine [see Adverse Reactions (6)].

Patients should be monitored for the development of peripheral neuropathy. Stavudine-related peripheral neuropathy may resolve if therapy is withdrawn promptly. If peripheral neuropathy develops permanent discontinuation of stavudine should be considered. In some cases, symptoms may worsen temporarily following discontinuation of therapy.

5.4 Pancreatitis

Fatal and nonfatal pancreatitis have occurred during therapy when stavudine was part of a combination regimen that included didanosine in both treatment-naive and treatment-experienced patients, regardless of degree of immunosuppression. The combination of stavudine and didanosine and any other agents that are toxic to the pancreas should be suspended in patients with suspected pancreatitis. Reinstitution of stavudine after a confirmed diagnosis of pancreatitis should be undertaken with particular caution and close patient monitoring; avoid use in combination with didanosine.

5.5 Fat Redistribution

Redistribution/accumulation of body fat including central obesity, dorsocervical fat enlargement (buffalo hump), peripheral wasting, facial wasting, breast enlargement and “cushingoid appearance” have been observed in patients receiving antiretroviral therapy.

In randomized controlled trials of treatment-naive patients, clinical lipoatrophy or lipodystrophy developed in a higher proportion of patients treated with stavudine compared to other nucleosides (tenofovir or abacavir). Dual energy x-ray absorptiometry (DEXA) scans demonstrated overall limb fat loss in stavudine-treated patients compared to limb fat gain or no gain in patients treated with other nucleosides (abacavir, tenofovir or zidovudine). The incidence and severity of lipoatrophy or lipodystrophy are cumulative over time with stavudine-containing regimens. In clinical trials, switching from stavudine to other nucleosides (tenofovir or abacavir) resulted in increases in limb fat with modest to no improvements in clinical lipoatrophy. Patients receiving stavudine should be monitored for symptoms or signs of lipoatrophy or lipodystrophy and questioned about body changes related to lipoatrophy or lipodystrophy. Given the potential risks of using stavudine including lipoatrophy or lipodystrophy, a benefit-risk assessment for each patient should be made and an alternative antiretroviral should be considered.

5.6 Immune Reconstitution Syndrome

Immune reconstitution syndrome has been reported in patients treated with combination antiretroviral therapy, including stavudine. During the initial phase of combination antiretroviral treatment, patients whose immune system responds may develop an inflammatory response to indolent or residual opportunistic infections (such as Mycobacterium avium infection, cytomegalovirus, Pneumocystis jiroveci pneumonia (PCP) or tuberculosis), which may necessitate further evaluation and treatment.

Autoimmune disorders (such as Graves’ disease, polymyositis and Guillain-Barré syndrome) have also been reported to occur in the setting of immune reconstitution; however, the time to onset is more variable and can occur many months after initiation of treatment.

6 ADVERSE REACTIONS

The following adverse reactions are discussed in greater detail in other sections of the labeling:

- lactic acidosis and severe hepatomegaly with steatosis [see Boxed Warning and Warnings and Precautions (5.1)]
- hepatic toxicity [see Warnings and Precautions (5.2)]
- neurologic symptoms and motor weakness [see Warnings and Precautions (5.3)]
- pancreatitis [see Boxed Warning and Warnings and Precautions (5.4)]
- lipoatrophy/lipodystrophy [see Warnings and Precautions (5.5)]

When stavudine is used in combination with other agents with similar toxicities, the incidence of adverse reactions may be higher than when stavudine is used alone.

6.1 Clinical Trial Experience in Adults

Because clinical trials are conducted under widely varying conditions, adverse reaction rates observed in the clinical trials of a drug cannot be directly compared to rates in the clinical trials of another drug and may not reflect the rates observed in clinical practice.

Selected adverse reactions that occurred in adult patients receiving stavudine in a controlled monotherapy study (Study AI455-019) are provided in Table 2.

Table 2: Selected Adverse Reactions in Study AI455-019 [The incidences reported included all severity grades and all reactions regardless of causality.] (Monotherapy)
Adverse Reaction | Percent (%)
Adverse Reaction | Stavudine [Median duration of stavudine therapy = 79 weeks; median duration of zidovudine therapy = 53 weeks]; (40 mg twice daily); (n = 412) | Zidovudine; (200 mg 3 times daily); (n = 402)
Headache | 54 | 49
Diarrhea | 50 | 44
Peripheral Neurologic; Symptoms/Neuropathy | 52 | 39
Rash | 40 | 35
Nausea and Vomiting | 39 | 44

Pancreatitis was observed in three of the 412 adult patients who received stavudine in study AI455-019.

Selected adverse reactions that occurred in antiretroviral-naive adult patients receiving stavudine from two controlled combination studies are provided in Table 3.

Table 3: Selected Adverse Reactions [The incidences reported included all severity grades and all reactions regardless of causality.] in START 1 and START 2 [START 2 compared two triple-combination regimens in 205 treatment-naive patients. Patients received either stavudine (40 mg twice daily) plus didanosine plus indinavir or zidovudine plus lamivudine plus indinavir.] Studies (Combination Therapy)
Adverse Reaction | Percent (%)
Adverse Reaction | START 1 |  | START 2
Adverse Reaction | Stavudine +; Lamivudine + Indinavir; (n = 100 [Duration of stavudine therapy = 48 weeks]) | Zidovudine +; Lamivudine + Indinavir; (n = 102) | Stavudine +; Didanosine + Indinavir; (n = 102) | Zidovudine + Lamivudine + Indinavir; (n = 103)
Nausea | 43 | 63 | 53 | 67
Diarrhea | 34 | 16 | 45 | 39
Headache | 25 | 26 | 46 | 37
Rash | 18 | 13 | 30 | 18
Vomiting | 18 | 33 | 30 | 35
Peripheral Neurologic; Symptoms/Neuropathy | 8 | 7 | 21 | 10

Selected laboratory abnormalities reported in a controlled monotherapy study (Study AI455-019) are provided in Table 4.

Table 4: Selected Laboratory Abnormalities in Study AI455-019 [Data presented for patients for whom laboratory evaluations were performed.] [Median duration of stavudine therapy = 79 weeks; median duration of zidovudine therapy = 53 weeks]
Parameter | Percent (%)
Parameter | Stavudine; (40 mg twice daily); (n = 412) | Zidovudine; (200 mg 3 times daily); (n = 402)
AST (SGOT) (> 5 x ULN) | 11 | 10
ALT (SGPT) (> 5 x ULN) | 13 | 11
Amylase (≥ 1.4 x ULN) | 14 | 13
ULN = upper limit of normal

Selected laboratory abnormalities reported in two controlled combination studies are provided in Tables 5 and 6.

Table 5: Selected Laboratory Abnormalities in START 1 and START 2 Studies (Grades 3 to 4)
Parameter | Percent (%)
Parameter | START 1 |  | START 2
Parameter | Stavudine + Lamivudine + Indinavir; (n = 100) | Zidovudine +; Lamivudine + Indinavir; (n = 102) | Stavudine +; Didanosine + Indinavir; (n = 102) | Zidovudine + Lamivudine +; Indinavir; (n = 103)
Bilirubin (> 2.6 x ULN) | 7 | 6 | 16 | 8
AST (SGOT) (> 5 x ULN) | 5 | 2 | 7 | 7
ALT (SGPT) (> 5 x ULN) | 6 | 2 | 8 | 5
GGT (> 5 x ULN) | 2 | 2 | 5 | 2
Lipase (> 2 x ULN) | 6 | 3 | 5 | 5
Amylase (> 2 x ULN) | 4 | < 1 | 8 | 2
ULN = upper limit of normal.

Table 6: Selected Laboratory Abnormalities in START 1 and START 2 Studies (All Grades)
Parameter | Percent (%)
Parameter | START 1 |  | START 2
Parameter | Stavudine +; Lamivudine + Indinavir; (n = 100) | Zidovudine +; Lamivudine + Indinavir; (n = 102) | Stavudine +; Didanosine + Indinavir; (n = 102) | Zidovudine +; Lamivudine + Indinavir; (n = 103)
Total Bilirubin | 65 | 60 | 68 | 55
AST (SGOT) | 42 | 20 | 53 | 20
ALT (SGPT) | 40 | 20 | 50 | 18
GGT | 15 | 8 | 28 | 12
Lipase | 27 | 12 | 26 | 19
Amylase | 21 | 19 | 31 | 17

6.2 Clinical Trial Experience in Pediatric Patients

Adverse reactions and serious laboratory abnormalities reported in pediatric patients from birth through adolescence during clinical trials were similar in type and frequency to those seen in adult patients [see Use in Specific Populations (8.4)].

6.3 Post-marketing Experience

The following adverse reactions have been identified during post-marketing use of stavudine. Because these reactions are reported voluntarily from a population of unknown size, it is not always possible to reliably estimate their frequency or establish a causal relationship to drug exposure. These reactions have been chosen for inclusion due to their seriousness, frequency of reporting, causal connection to stavudine, or a combination of these factors.

Body as a Whole: abdominal pain, allergic reaction, chills/fever and redistribution/accumulation of body fat [see Warnings and Precautions (5.5)].

Digestive Disorders: anorexia.

Exocrine Gland Disorders: pancreatitis, including fatal cases [see Warnings and Precautions (5.4)].

Hematologic Disorders: anemia, leukopenia, thrombocytopenia, neutropenia and macrocytosis.

Liver: symptomatic hyperlactatemia/lactic acidosis and hepatic steatosis [see Warnings and Precautions (5.1)], hepatitis and liver failure.

Metabolic Disorders: lipoatrophy, lipodystrophy [see Warnings and Precautions (5.5)], diabetes mellitus and hyperglycemia.

Musculoskeletal: myalgia.

Nervous System: insomnia, severe motor weakness (most often reported in the setting of lactic acidosis) [see Warnings and Precautions (5.1, 5.3)].

Use with Didanosine- and Hydroxyurea-based Regimens

When stavudine is used in combination with other agents with similar toxicities, the incidence of these toxicities may be higher than when stavudine is used alone. Thus, patients treated with stavudine in combination with didanosine, with or without hydroxyurea, may be at increased risk for pancreatitis and hepatotoxicity, which may be fatal, and severe peripheral neuropathy [see Warnings and Precautions (5)]. The combination of stavudine and hydroxyurea, with or without didanosine, should be avoided.

7 DRUG INTERACTIONS

Stavudine is unlikely to interact with drugs metabolized by cytochrome P450 isoenzymes.

Zidovudine: Zidovudine competitively inhibits the intracellular phosphorylation of stavudine. Therefore, use of zidovudine in combination with stavudine should be avoided.

Doxorubicin: In vitro data indicate that the phosphorylation of stavudine is inhibited at relevant concentrations by doxorubicin. The clinical significance of this interaction is unknown; therefore, concomitant use of stavudine with doxorubicin should be undertaken with caution.

Ribavirin: In vitro data indicate ribavirin reduces phosphorylation of lamivudine, stavudine and zidovudine. The clinical significance of the interaction with stavudine is unknown; therefore, concomitant use of stavudine with ribavirin should be undertaken with caution. No pharmacokinetic (e.g., plasma concentrations or intracellular triphosphorylated active metabolite concentrations) or pharmacodynamic (e.g., loss of HIV-1/HCV virologic suppression) interaction was observed when ribavirin and lamivudine (n = 18), stavudine (n = 10) or zidovudine (n = 6) were coadministered as part of a multi-drug regimen to HIV-1/HCV co-infected patients [see Warnings and Precautions (5.2)].

USE IN SPECIFIC POPULATIONS

Pregnancy Category C

Reproduction studies have been performed in rats and rabbits with exposures (based on Cmax) up to 399 and 183 times, respectively, of that seen at a clinical dosage of 1 mg/kg/day and have revealed no evidence of teratogenicity. The incidence in fetuses of a common skeletal variation, unossified or incomplete ossification of sternebra, was increased in rats at 399 times human exposure, while no effect was observed at 216 times human exposure. A slight post-implantation loss was noted at 216 times the human exposure with no effect noted at approximately 135 times the human exposure. An increase in early rat neonatal mortality (birth to 4 days of age) occurred at 399 times the human exposure, while survival of neonates was unaffected at approximately 135 times the human exposure. A study in rats showed that stavudine is transferred to the fetus through the placenta. The concentration in fetal tissue was approximately one-half the concentration in maternal plasma. Animal reproduction studies are not always predictive of human response.

There are no adequate and well controlled studies of stavudine in pregnant women. Stavudine should be used during pregnancy only if the potential benefit justifies the potential risk.

Fatal lactic acidosis has been reported in pregnant women who received the combination of stavudine and didanosine with other antiretroviral agents. It is unclear if pregnancy augments the risk of lactic acidosis/hepatic steatosis syndrome reported in nonpregnant individuals receiving nucleoside analogues [see Boxed Warning and Warnings and Precautions (5.1)]. The combination of stavudine and didanosine should be used with caution during pregnancy and is recommended only if the potential benefit clearly outweighs the potential risk. Healthcare providers caring for HIV-infected pregnant women receiving stavudine should be alert for early diagnosis of lactic acidosis/hepatic steatosis syndrome.

Antiretroviral Pregnancy Registry

To monitor maternal-fetal outcomes of pregnant women exposed to stavudine and other antiretroviral agents, an Antiretroviral Pregnancy Registry has been established. Physicians are encouraged to register patients by calling 1-800-258-4263.

8.3 Nursing Mothers

The Centers for Disease Control and Prevention recommend that HIV-infected mothers not breast-feed their infants to avoid risking postnatal transmission of HIV. Studies in lactating rats demonstrated that stavudine is excreted in milk. Although it is not known whether stavudine is excreted in human milk, there exists the potential for adverse effects from stavudine in nursing infants. Because of both the potential for HIV transmission and the potential for serious adverse reactions in nursing infants, mothers should be instructed not to breast-feed if they are receiving stavudine.

8.4 Pediatric Use

Use of stavudine in pediatric patients from birth through adolescence is supported by evidence from adequate and well controlled studies of stavudine in adults with additional pharmacokinetic and safety data in pediatric patients [see Dosage and Administration (2.2) and Adverse Reactions (6.2)].

Adverse reactions and laboratory abnormalities reported to occur in pediatric patients in clinical studies were generally consistent with the safety profile of stavudine in adults. These studies include ACTG 240, where 105 pediatric patients ages 3 months to 6 years received stavudine 2 mg/kg/day for a median of 6.4 months; a controlled clinical trial where 185 newborns received stavudine 2 mg/kg/day either alone or in combination with didanosine from birth through 6 weeks of age; and a clinical trial where 8 newborns received stavudine 2 mg/kg/day in combination with didanosine and nelfinavir from birth through 4 weeks of age.

Stavudine pharmacokinetics have been evaluated in 25 HIV-1-infected pediatric patients ranging in age from 5 weeks to 15 years and in weight from 2 to 43 kg after IV or oral administration of single doses and twice-daily regimens and in 30 HIV-1-exposed or -infected newborns ranging in age from birth to 4 weeks after oral administration of twice-daily regimens [see Clinical Pharmacology (12.3, Table 9)].

8.5 Geriatric Use

Clinical studies of stavudine did not include sufficient numbers of patients aged 65 years and over to determine whether they respond differently than younger patients. Greater sensitivity of some older individuals to the effects of stavudine cannot be ruled out.

In a monotherapy Expanded Access Program for patients with advanced HIV-1 infection, peripheral neuropathy or peripheral neuropathic symptoms were observed in 15 of 40 (38%) elderly patients receiving 40 mg twice daily and 8 of 51 (16%) elderly patients receiving 20 mg twice daily. Of the approximately 12,000 patients enrolled in the Expanded Access Program, peripheral neuropathy or peripheral neuropathic symptoms developed in 30% of patients receiving 40 mg twice daily and 25% of patients receiving 20 mg twice daily. Elderly patients should be closely monitored for signs and symptoms of peripheral neuropathy.

Stavudine is known to be substantially excreted by the kidney, and the risk of toxic reactions to this drug may be greater in patients with impaired renal function. Because elderly patients are more likely to have decreased renal function, it may be useful to monitor renal function. Dose adjustment is recommended for patients with renal impairment [see Dosage and Administration (2.3)].

8.6 Renal Impairment

Data from two studies in adults indicated that the apparent oral clearance of stavudine decreased and the terminal elimination half-life increased as creatinine clearance decreased. Based on these observations, it is recommended that the stavudine dosage be modified in patients with reduced creatinine clearance and in patients receiving maintenance hemodialysis [see Dosage and Administration (2.3) and Clinical Pharmacology (12.3)].

10 OVERDOSAGE

Experience with adults treated with 12 to 24 times the recommended daily dosage revealed no acute toxicity. Complications of chronic overdosage include peripheral neuropathy and hepatic toxicity. Stavudine can be removed by hemodialysis; the mean ± SD hemodialysis clearance of stavudine is 120 ± 18 mL/min. Whether stavudine is eliminated by peritoneal dialysis has not been studied.

11 DESCRIPTION

Stavudine (d4T) is a synthetic thymidine nucleoside analogue, active against the human immunodeficiency virus type 1 (HIV-1). The chemical name for stavudine is 2',3'-didehydro-3'-deoxythymidine. Stavudine has the following structural formula:

Stavudine, USP is a white to off-white crystalline solid with the molecular formula C10H12N2O4 and a molecular weight of 224.21. The solubility of stavudine at 23°C is approximately 83 mg/mL in water and 30 mg/mL in propylene glycol. The n-octanol/water partition coefficient of stavudine at 23°C is 0.144.

Stavudine Capsules, USP are supplied for oral administration in strengths of 15 mg, 20 mg, 30 mg or 40 mg of stavudine, USP. Each capsule also contains inactive ingredients: lactose anhydrous, magnesium stearate, microcrystalline cellulose and sodium starch glycolate. The empty hard shell gelatin capsules contain gelatin and titanium dioxide. In addition, the 15 mg empty capsules contain D&C Red No. 28, D&C Yellow No. 10, FD&C Blue No. 1, FD&C Red No. 40, FD&C Yellow No. 6; the 20 mg empty capsules contain D&C Red No. 28, FD&C Blue No. 1, FD&C Red No. 40; the 30 mg empty capsules contain D&C Red No. 28, D&C Yellow No. 10, FD&C Red No. 40, FD&C Yellow No. 6; and the 40 mg empty capsules contain D&C Red No. 28, D&C Yellow No. 10, FD&C Yellow No. 6.

The imprinting ink contains black iron oxide, potassium hydroxide, propylene glycol and shellac.

12 CLINICAL PHARMACOLOGY

12.1 Mechanism of Action

Stavudine is an antiviral drug [see Clinical Pharmacology (12.4)].

12.3 Pharmacokinetics

The pharmacokinetics of stavudine have been evaluated in HIV-1-infected adult and pediatric patients (Tables 7, 8, and 9). Peak plasma concentrations (Cmax) and area under the plasma concentration-time curve (AUC) increased in proportion to dose after both single and multiple doses ranging from 0.03 to 4 mg/kg. There was no significant accumulation of stavudine with repeated administration every 6, 8, or 12 hours.

Absorption

Following oral administration, stavudine is rapidly absorbed, with peak plasma concentrations occurring within one hour after dosing. The systemic exposure to stavudine is the same following administration as capsules or solution. Steady-state pharmacokinetic parameters of stavudine in HIV-1-infected adults are shown in Table 7.

Table 7: Steady-State Pharmacokinetic Parameters of Stavudine in HIV-1-Infected
Parameter | Stavudine; 40 mg BID; Mean ± SD (n = 8)
AUC0-24 (ng•h/mL); Cmax (ng/mL); Cmin (ng/mL) | 2568 ± 454; 536 ± 146; 8 ± 9
AUC0-24 = Area under the curve over 24 hours
Cmax = Maximum plasma concentration
Cmin = Trough or minimum plasma concentration

Distribution

Binding of stavudine to serum proteins was negligible over the concentration range of 0.01 to 11.4 mcg/mL. Stavudine distributes equally between red blood cells and plasma. Volume of distribution is shown in Table 8.

Metabolism

Metabolism plays a limited role in the clearance of stavudine. Unchanged stavudine was the major drug-related component circulating in plasma after an 80 mg dose of ^14C-stavudine, while metabolites constituted minor components of the circulating radioactivity. Minor metabolites include oxidized stavudine, glucuronide conjugates of stavudine and its oxidized metabolite, and an N-acetylcysteine conjugate of the ribose after glycosidic cleavage, suggesting that thymine is also a metabolite of stavudine.

Elimination

Following an 80 mg dose of ^14C-stavudine to healthy subjects, approximately 95% and 3% of the total radioactivity was recovered in urine and feces, respectively. Radioactivity due to parent drug in urine and feces was 73.7% and 62%, respectively. The mean terminal elimination half-life is approximately 2.3 hours following single oral doses. Mean renal clearance of the parent compound is approximately 272 mL/min, accounting for approximately 67% of the apparent oral clearance.

In HIV-1-infected patients, renal elimination of unchanged drug accounts for about 40% of the overall clearance regardless of the route of administration (Table 8). The mean renal clearance was about twice the average endogenous creatinine clearance, indicating active tubular secretion in addition to glomerular filtration.

Table 8: Pharmacokinetic Parameters of Stavudine in HIV-1-Infected Adults: Bioavailability, Distribution and Clearance
Parameter | Mean ± SD | n
Oral bioavailability (%) | 86.4 ± 18.2 | 25
Volume of distribution (L) [Following 1-hour IV infusion] | 46 ± 21 | 44
Total body clearance (mL/min) | 594 ± 164 | 44
Apparent oral clearance (mL/min) [Following single oral dose] | 560 ± 182 [Assuming a body weight of 70 kg] | 113
Renal clearance (mL/min) | 237 ± 98 | 39
Elimination half-life, IV dose (h) | 1.15 ± 0.35 | 44
Elimination half-life, oral dose (h) | 1.6 ± 0.23 | 8
Urinary recovery of stavudine (% of dose) [Over 12 to 24 hours] | 42 ± 14 | 39

Pediatric

Pharmacokinetic properties of stavudine in pediatric patients are presented in Table 9.

Table 9: Pharmacokinetic Parameters (Mean ± SD) of Stavudine in HIV-1-Exposed or -Infected Pediatric Patients
Parameter | Ages 5 weeks; to 15 years | n | Ages 14; to 28 days | n | Day of Birth | n
Oral bioavailability (%) | 76.9 ± 31.7 | 20 | ND |  | ND
Volume of distribution (L/kg) [Following 1-hour IV infusion.] | 0.73 ± 0.32 | 21 | ND |  | ND
Ratio of CSF:plasma; concentrations (as %) [At median time of 2.5 hours (range 2 to 3 hours) following multiple oral doses.] | 59 ± 35 | 8 | ND |  | ND
Total body clearance; (mL/min/kg) | 9.75 ± 3.76 | 21 | ND |  | ND
Apparent oral clearance; (mL/min/kg) [Following single oral dose.] | 13.75 ± 4.29 | 20 | 11.52 ± 5.93 | 30 | 5.08 ± 2.80 | 17
Elimination half-life, IV dose (h) | 1.11 ± 0.28 | 21 | ND |  | ND
Elimination half-life, oral dose (h) | 0.96 ± 0.26 | 20 | 1.59 ± 0.29 | 30 | 5.27 ± 2.01 | 17
Urinary recovery of stavudine; (% of dose) [Over 8 hours.] | 34 ± 16 | 19 | ND |  | ND
ND = Not determined.

Renal Impairment

Data from two studies in adults indicated that the apparent oral clearance of stavudine decreased and the terminal elimination half-life increased as creatinine clearance decreased (see Table 10). Cmax and Tmax were not significantly altered by renal impairment. The mean ± SD hemodialysis clearance value of stavudine was 120 ± 18 mL/min (n = 12); the mean ± SD percentage of the stavudine dose recovered in the dialysate, timed to occur between 2 to 6 hours post-dose, was 31 ± 5%. Based on these observations, it is recommended that stavudine dosage be modified in patients with reduced creatinine clearance and in patients receiving maintenance hemodialysis [see Dosage and Administration (2.3)].

Table 10: Mean ± SD Pharmacokinetic Parameter Values of Stavudine [Single 40 mg oral dose] in Adults with Varying Degrees of Renal Function
 | Creatinine Clearance |  |  | Hemodialysis Patients [Determined while patients were off dialysis]; (n = 11)
 | > 50 mL/min; (n = 10) | 26 to 50 mL/min; (n = 5) | 9 to 25 mL/min; (n = 5) | Hemodialysis Patients [Determined while patients were off dialysis]; (n = 11)
Creatinine clearance (mL/min) | 104 ± 28 | 41 ± 5 | 17 ± 3 | NA
Apparent oral clearance (mL/min) | 335 ± 57 | 191 ± 39 | 116 ± 25 | 105 ± 17
Renal clearance (mL/min) | 167 ± 65 | 73 ± 18 | 17 ± 3 | NA
T1/2 (h) | 1.7 ± 0.4 | 3.5 ± 2.5 | 4.6 ± 0.9 | 5.4 ± 1.4
T1/2 = Terminal elimination half-life
NA = Not applicable

Hepatic Impairment

Stavudine pharmacokinetics were not altered in five non-HIV-infected patients with hepatic impairment secondary to cirrhosis (Child-Pugh classification B or C) following the administration of a single 40 mg dose.

Geriatric

Stavudine pharmacokinetics have not been studied in patients > 65 years of age [see Use in Specific Populations (8.5)].

Gender

A population pharmacokinetic analysis of data collected during a controlled clinical study in HIV-1-infected patients showed no clinically important differences between males (n = 291) and females (n = 27).

Race

A population pharmacokinetic analysis of data collected during a controlled clinical study in HIV-1-infected patients showed no clinically important differences between races (n = 233 Caucasian, 39 African-American, 41 Hispanic, 1 Asian and 4 other).

Drug Interaction Studies

Stavudine does not inhibit the major cytochrome P450 isoforms CYP1A2, CYP2C9, CYP2C19, CYP2D6 and CYP3A4; therefore, it is unlikely that clinically significant drug interactions will occur with drugs metabolized through these pathways. Because stavudine is not protein bound, it is not expected to affect the pharmacokinetics of protein bound drugs.

Tables 11 and 12 summarize the effects on AUC and Cmax, with a 95% confidence interval (CI) when available, following coadministration of stavudine with didanosine, lamivudine and nelfinavir. No clinically significant pharmacokinetic interactions were observed.

Table 11: Results of Drug Interaction Studies with Stavudine: Effects of Coadministered Drug on Stavudine Plasma AUC and Cmax Values
Drug | Stavudine; Dosage | n [HIV-1-infected patients] | AUC of Stavudine; (95% CI) | Cmax of Stavudine; (95% CI)
Didanosine, 100 mg q12h for 4 days | 40 mg q12h for 4 days | 10 | ↔ | ↑17%
Lamivudine, 150 mg single dose | 40 mg single dose | 18 | ↔; (92.7% to 100.6%) | ↑12%; (100.3% to 126.1%)
Nelfinavir, 750 mg q8h for 56 days | 30 to 40 mg q12h for 56 days | 8 | ↔ | ↔
↑ Indicates increase.
↔ Indicates no change, or mean increase or decrease of < 10%

Table 12: Results of Drug Interaction Studies with Stavudine: Effects of Stavudine on Coadministered Drug Plasma AUC and Cmax Values
Drug | Stavudine; Dosage | n [HIV-1-infected patients] | AUC of Coadministered Drug; (95% CI) | Cmax of Coadministered Drug; (95% CI)
Didanosine, 100 mg q12h for 4 days | 40 mg q12h; for 4 days | 10 | ↔ | ↔
Lamivudine, 150 mg single dose | 40 mg single dose | 18 | ↔; (90.5% to 107.6%) | ↔; (87.1% to 110.6%)
Nelfinavir, 750 mg q8h for 56 days | 30 to 40 mg q12h; for 56 days | 8 | ↔ | ↔
↔ Indicates no change, or mean increase or decrease of < 10%.

Mechanism of Action

Stavudine, a nucleoside analogue of thymidine, is phosphorylated by cellular kinases to the active metabolite stavudine triphosphate. Stavudine triphosphate inhibits the activity of HIV-1 reverse transcriptase (RT) by competing with the natural substrate thymidine triphosphate (Ki = 0.0083 to 0.032 µM) and by causing DNA chain termination following its incorporation into viral DNA. Stavudine triphosphate inhibits cellular DNA polymerases β and γ and markedly reduces the synthesis of mitochondrial DNA.

Antiviral Activity in Cell Culture

The cell culture antiviral activity of stavudine was measured in peripheral blood mononuclear cells, monocytic cells, and lymphoblastoid cell lines. The concentration of drug necessary to inhibit HIV-1 replication by 50% (EC50) ranged from 0.009 to 4 µM against laboratory and clinical isolates of HIV-1. In cell culture, stavudine exhibited additive to antagonistic activity in combination with zidovudine. Stavudine in combination with either abacavir, didanosine, tenofovir or zalcitabine exhibited additive to synergistic anti-HIV-1 activity. Ribavirin, at the 9 to 45 µM concentrations tested, reduced the anti-HIV-1 activity of stavudine by 2.5- to 5-fold. The relationship between cell culture susceptibility of HIV-1 to stavudine and the inhibition of HIV-1 replication in humans has not been established.

Resistance

HIV-1 isolates with reduced susceptibility to stavudine have been selected in cell culture (strain-specific) and were also obtained from patients treated with stavudine. Phenotypic analysis of HIV-1 isolates from 61 patients receiving prolonged (6 to 29 months) stavudine monotherapy showed that post-therapy isolates from four patients exhibited EC50 values more than 4-fold (range 7- to 16-fold) higher than the average pretreatment susceptibility of baseline isolates. Of these, HIV-1 isolates from one patient contained the zidovudine-resistance-associated substitutions T215Y and K219E, and isolates from another patient contained the multiple-nucleoside-resistance-associated substitution Q151M. Mutations in the RT gene of HIV-1 isolates from the other two patients were not detected. The genetic basis for stavudine susceptibility changes has not been identified.

Cross-resistance

Cross-resistance among HIV-1 reverse transcriptase inhibitors has been observed. Several studies have demonstrated that prolonged stavudine treatment can select and/or maintain thymidine analogue mutations (TAMs; M41L, D67N, K70R, L210W, T215Y/F, K219Q/E) associated with zidovudine resistance. HIV-1 isolates with one or more TAMs exhibited reduced susceptibility to stavudine in cell culture. These TAMs are seen at a similar frequency with stavudine and zidovudine in virological treatment. The clinical relevance of these findings suggests that stavudine should be avoided in the presence of thymidine analogue mutations.

13 NONCLINICAL TOXICOLOGY

13.1 Carcinogenesis, Mutagenesis, Impairment of Fertility

In 2-year carcinogenicity studies in mice and rats, stavudine was noncarcinogenic at doses which produced exposures (AUC) 39 and 168 times, respectively, human exposure at the recommended clinical dose. Benign and malignant liver tumors in mice and rats and malignant urinary bladder tumors in male rats occurred at levels of exposure 250 (mice) and 732 (rats) times human exposure at the recommended clinical dose.

Stavudine was not mutagenic in the Ames, E. coli reverse mutation, or the CHO/HGPRT mammalian cell forward gene mutation assays, with and without metabolic activation. Stavudine produced positive results in the in vitro human lymphocyte clastogenesis and mouse fibroblast assays, and in the in vivo mouse micronucleus test. In the in vitro assays, stavudine elevated the frequency of chromosome aberrations in human lymphocytes (concentrations of 25 to 250 mcg/mL, without metabolic activation) and increased the frequency of transformed foci in mouse fibroblast cells (concentrations of 25 to 2500 mcg/mL, with and without metabolic activation). In the in vivo micronucleus assay, stavudine was clastogenic in bone marrow cells following oral stavudine administration to mice at dosages of 600 to 2000 mg/kg/day for 3 days.

No evidence of impaired fertility was seen in rats with exposures (based on Cmax) up to 216 times that observed following a clinical dosage of 1 mg/kg/day.

14 CLINICAL STUDIES

Combination Therapy

The combination use of stavudine is based on the results of clinical studies in HIV-1-infected patients in double- and triple-combination regimens with other antiretroviral agents.

One of these studies (START 1) was a multicenter, randomized, open-label study comparing stavudine (40 mg twice daily) plus lamivudine plus indinavir to zidovudine plus lamivudine plus indinavir in 202 treatment-naive patients. Both regimens resulted in a similar magnitude of inhibition of HIV-1 RNA levels and increases in CD4^+ cell counts through 48 weeks.

Monotherapy

The efficacy of stavudine was demonstrated in a randomized, double-blind study (AI455-019, conducted 1992 to 1994) comparing stavudine with zidovudine in 822 patients with a spectrum of HIV-1-related symptoms. The outcome in terms of progression of HIV-1 disease and death was similar for both drugs.

16 HOW SUPPLIED/STORAGE AND HANDLING

16.1 Capsules

Stavudine Capsules, USP are available containing 15 mg, 20 mg, 30 mg or 40 mg of stavudine, USP.

The 15 mg capsules have a hard-shell gelatin capsule with an off-white opaque cap and a pink opaque body filled with a white to off-white powder. The capsule is axially printed with M 154 in black ink on both the cap and body.

The 20 mg capsules have a hard-shell gelatin capsule with a pink opaque cap and a pink opaque body filled with a white to off-white powder. The capsule is axially printed with M 155 in black ink on both the cap and body.

The 30 mg capsules have a hard-shell gelatin capsule with an off-white opaque cap and a light orange opaque body filled with a white to off-white powder. The capsule is axially printed with M 137 in black ink on both the cap and body.

The 40 mg capsules have a hard-shell gelatin capsule with a light orange opaque cap and a light orange opaque body filled with a white to off-white powder. The capsule is axially printed with M 138 in black ink on both the cap and body.

They are supplied by State of Florida DOH Central Pharmacy as follows:

NDC | Strength | Quantity/Form | Color | Source Prod. Code
53808-0852-1 | 20 mg | 30 Capsules in a Blister Pack | pink opaque | 0378-5041

16.3 Storage

Store at 20° to 25°C (68° to 77°F). [See USP Controlled Room Temperature.]

Dispense in a tight, light-resistant container as defined in the USP using a child-resistant closure.

PHARMACIST: Dispense a Medication Guide with each prescription.

17 PATIENT COUNSELING INFORMATION

See MEDICATION GUIDE.

17.1 General

Patients should be advised that stavudine capsules are not a cure for HIV-1 infection, and that they may continue to experience illnesses associated with HIV-1 infection, including opportunistic infections. Patients should be advised to remain under the care of a physician when using stavudine capsules and the importance of adherence to any antiretroviral regimen including those that contain stavudine capsules.

Patients should be advised to avoid doing things that can spread HIV-1 infection to others.

- Do not share needles or other injection equipment.
- Do not share personal items that can have blood or body fluids on them, like toothbrushes and razor blades.
- Do not have any kind of sex without protection. Always practice safe sex by using a latex or polyurethane condom or other barrier method to lower the chance of sexual contact with semen, vaginal secretions or blood.
- Do not breast-feed. It is not known if stavudine can be passed to your baby in your breast milk and whether it could harm your baby. Also, mothers with HIV-1 should not breast-feed because HIV-1 can be passed to the baby in breast milk.

Patients should be informed that when stavudine capsules are used in combination with other agents with similar toxicities, the incidence of adverse reactions may be higher than when stavudine capsules are used alone.

Patients should be instructed that if they miss a dose, to take it as soon as possible. If it is almost time for the next dose, skip the missed dose and continue the regular dosing schedule.

Patients should be instructed if they take too much stavudine capsules, they should contact a poison control center or emergency room right away.

Patients should be informed that the Centers for Disease Control and Prevention (CDC) recommend that HIV-infected mothers not nurse newborn infants to reduce the risk of postnatal transmission of HIV infection.

17.2 Lactic Acidosis

Patients should be informed of the importance of early recognition of symptoms of symptomatic hyperlactatemia or lactic acidosis syndrome, which include unexplained weight loss, abdominal discomfort, nausea, vomiting, fatigue, dyspnea and motor weakness. Patients in whom these symptoms develop should seek medical attention immediately. Discontinuation of stavudine capsule therapy may be required.

17.3 Hepatic Toxicity

Patients should be informed that an increased risk of hepatotoxicity, which may be fatal, may occur in patients treated with stavudine capsules in combination with didanosine and hydroxyurea. This combination should be avoided.

17.4 Peripheral Neuropathy

Patients should be informed that an important toxicity of stavudine is peripheral neuropathy. Patients should be aware that peripheral neuropathy is manifested by numbness, tingling, or pain in hands or feet, and that these symptoms should be reported to their physicians. Patients should be counseled that peripheral neuropathy occurs with greatest frequency in patients who have advanced HIV-1 disease or a history of peripheral neuropathy, and discontinuation of stavudine capsules may be required if toxicity develops.

Caregivers of young children receiving stavudine capsule therapy should be instructed regarding detection and reporting of peripheral neuropathy.

17.5 Pancreatitis

Patients should be informed that an increased risk of pancreatitis, which may be fatal, may occur in patients treated with the combination of stavudine capsules and didanosine. This combination should be avoided. Patients should be closely monitored for symptoms of pancreatitis.

The patient should be instructed to avoid alcohol while taking stavudine capsules. Alcohol may increase the patient’s risk of pancreatitis or liver damage.

17.6 Fat Redistribution

Patients should be informed that redistribution or accumulation of body fat may occur in individuals receiving antiretroviral therapy including stavudine capsules. Patients receiving stavudine capsules should be monitored for clinical signs and symptoms of lipoatrophy/lipodystrophy. Patients should be routinely questioned about body changes related to lipoatrophy/lipodystrophy.

MEDICATION GUIDE
STAVUDINE CAPSULES, USP

15 mg, 20 mg, 30 mg and 40 mg
(stavudine, also known as d4T)
(stav' ue deen)

Read this Medication Guide before you start taking stavudine capsules and each time you get a refill. There may be new information. This information does not take the place of talking with your healthcare provider about your medical condition or your treatment. You and your healthcare provider should talk about your treatment with stavudine capsules before you start taking it and at regular check-ups. You should stay under your healthcare provider’s care when taking stavudine capsules.

What is the most important information I should know about stavudine capsules?

Stavudine capsules can cause serious side effects, including:

1. Build up of acid in your blood (lactic acidosis). Lactic acidosis can cause death and must be treated in the hospital. The risk of lactic acidosis may be higher if you:
  - have liver problems
  - are pregnant. There have been deaths reported in pregnant women who get lactic acidosis after taking stavudine capsules and VIDEX®†, or stavudine capsules and VIDEX EC®† (didanosine).
  - are female
  - are overweight
  - have been treated for a long time with other medicines used to treat HIV
  It is important to call your healthcare provider right away if you:
  - feel weak or tired
  - have unusual (not normal) muscle pain
  - have trouble breathing
  - have stomach pain with nausea and vomiting
  - feel cold, especially in your arms and legs
  - feel dizzy or light-headed
  - have a fast or irregular heartbeat
2. Liver problems. Some people (including pregnant women) who have taken stavudine capsules have had serious liver problems. These problems include liver enlargement (hepatomegaly), fat in the liver (steatosis), liver failure and death due to liver problems. Your healthcare provider should check your liver function while you are taking stavudine capsules. You should be especially careful if you have a history of heavy alcohol use or liver problems. Use of stavudine capsules with VIDEX EC®† or VIDEX®† (didanosine) may increase your risk for liver damage.
  It is important to call your healthcare provider right away if you have:
  - yellowing of your skin or the white of your eyes (jaundice)
  - dark urine
  - pain on the right side of your stomach
  - swelling of your stomach
  - easy bruising or bleeding
  - loss of appetite
  - nausea or vomiting
3. Swelling of the pancreas (pancreatitis) that may cause death has occurred when stavudine capsules was used with VIDEX EC®† or VIDEX®† (didanosine). Pancreatitis can happen at any time during your treatment with stavudine capsules.
  It is important to call your healthcare provider right away if you have:
  - stomach pain
  - swelling of your stomach
  - nausea and vomiting
  - fever

What are stavudine capsules?

Stavudine capsules are a prescription medicine used with other HIV medicines to treat human immunodeficiency virus (HIV) infection in children and adults. Stavudine capsules belong to a class of drugs called nucleoside analogues.

Stavudine capsules will not cure your HIV infection. At present there is no cure for HIV infection. Even while taking stavudine capsules, you may continue to have HIV-related illnesses, including infections with other disease-producing organisms. Continue to see your healthcare provider regularly and report any medical problems that occur.

Who should not take stavudine capsules?

Do not take stavudine capsules if you:

- are allergic to stavudine or any of the ingredients in stavudine capsules. See the end of this Medication Guide for a complete list of the ingredients in stavudine capsules.

What should I tell my healthcare provider before taking stavudine capsules?

Before you take stavudine capsules, tell your healthcare provider if you:

- have or had liver problems (such as hepatitis)
- have or had problems with your pancreas (pancreatitis)
- have or had kidney problems
- have or had persistent numbness, tingling or pain in the hands or feet (neuropathy)
- have gallstones
- drink alcoholic beverages
- have any other medical conditions
- are pregnant or plan to become pregnant. It is not known if stavudine capsules will harm your unborn baby. Tell your healthcare provider right away if you become pregnant while taking stavudine capsules. You and your healthcare provider will decide if you should take stavudine capsules while you are pregnant.
  Pregnancy Registry: There is a pregnancy registry for women who take antiviral medicines during pregnancy. The purpose of the registry is to collect information about the health of you and your baby. Talk to your healthcare provider about how you can take part in this registry.
- are breast-feeding or plan to breast-feed. Do not breast-feed. It is not known if stavudine can be passed to your baby in your breast milk and whether it could harm your baby. Also, mothers with HIV-1 should not breast-feed because HIV-1 can be passed to the baby in the breast milk.

Tell your healthcare provider about all the medicines that you take, including prescription and non-prescription medicines, vitamins or herbal supplements. Stavudine capsules may affect the way other medicines work, and other medicines may affect how stavudine capsules work.

Especially tell your healthcare provider if you take:

- COMBIVIR®†, RETROVIR®†, TRIZIVIR®† (zidovudine or AZT)
- VIDEX®† or VIDEX EC®† (didanosine)
- ADRIAMYCIN®†, RUBEX®† (doxorubicin)
- COPEGUS®†, REBETOL®†, RIBASPHERE®†, RIBAVIRIN®†, VIRAZOLE®† (ribavirin)
- ROFERON-A®† , INTRON-A®† and others (interferon)
- HYDREA®† , DROXIA®† (hydroxyurea)

Know the medicines you take. Keep a list of your medicines and show it to your healthcare provider and pharmacist when you get a new medicine.

Ask your healthcare provider if you are not sure if you take one of the medicines listed above.

How should I take stavudine capsules?

- Take stavudine capsules exactly as your healthcare provider tells you to take it.
- Your healthcare provider will tell you how much stavudine capsules to take and when to take it.
- If your child will be taking stavudine capsules, your child’s healthcare provider should give you instructions on how to give this medicine.
- Your healthcare provider may change your dose. Do not change your dose of stavudine capsules without talking to your healthcare provider.
- Stavudine capsules may be taken with or without food.
- Try not to miss a dose, but if you do, take it as soon as possible. If it is almost time for the next dose, skip the missed dose and continue your regular dosing schedule.
- Some medicines may require your healthcare provider to monitor your therapy or change your therapy. Check with your healthcare provider.
- If your kidneys are not working well, your healthcare provider will need to do regular blood and urine tests to check how they are working while you take stavudine capsules. Your healthcare provider may also lower your dosage of stavudine capsules if your kidneys are not working well.
- If you take too much stavudine capsules, contact a poison control center or emergency room right away.

What should I avoid while taking stavudine capsules?

- Alcohol. You should avoid drinking alcohol while taking stavudine capsules. Alcohol may increase your risk of getting pain and swelling of your pancreas (pancreatitis) or may damage your liver.

What are the possible side effects of stavudine capsules?

Stavudine capsules can cause serious side effects including:

- Stavudine capsules can cause lactic acidosis, liver problems and pancreatitis. See “What is the most important information I should know about stavudine capsules?”
- Neurologic symptoms. Symptoms include: weakness of your legs, feet, arms or hands (motor weakness) and numbness or tingling in your hands or feet (neuropathy). These problems can happen more often in people who have advanced HIV disease, have a history of peripheral neuropathy, or in people who take other medicines that also are associated with neuropathy including didanosine. In some cases, neuropathy may temporarily worsen after you stop taking stavudine capsules. Neuropathy can be difficult to notice in children who take stavudine capsules. Ask you child’s healthcare provider for the signs and symptoms of peripheral neuropathy in children.
  It is important to call your healthcare provider right away if you have:
  - numbness in your hands or feet
  - tingling in your hands or feet
  - weakness in your legs, feet, arms, or hands
- Changes in body fat (fat redistribution). Changes in body fat (lipoatrophy or lipodystrophy) have been seen in some people taking HIV medicines including stavudine capsules. Loss of body fat (lipoatrophy) happens more often in people who take stavudine capsules than in people who take other similar HIV medicines.
  These changes may include:
  - more fat in or around your
    - trunk
    - upper back and neck (buffalo hump)
    - breast or chest
  - loss of fat in your
    - legs
    - arms
    - face
  Your healthcare provider will monitor you for changes in your body fat. It is important to tell your healthcare provider if you notice any of these changes.
- Changes in your immune system (immune reconstitution syndrome). Your immune system may begin to fight infections that have been in your body for a long time. Tell your healthcare provider if you start having new or worse symptoms of infection after you start taking HIV medicine.

The most common side effects of stavudine capsules include:

- headache
- diarrhea
- rash
- nausea
- vomiting

Tell your healthcare provider if you have any side effect that bothers you or that does not go away.

These are not all the possible side effects of stavudine capsules. For more information, ask your healthcare provider or pharmacist.

Call your doctor for medical advice about side effects. You may report side effects to FDA at 1-800-FDA-1088.

How should I store stavudine capsules?

Store stavudine capsules in a tightly closed container at room temperature at 20° to 25°C (68° to 77°F).

Keep stavudine capsules and all medicines out of the reach of children and pets.

General Information about the safe and effective use of stavudine capsules.

Avoid doing things that can spread HIV-1 infection to others.

- Do not share needles or other injection equipment.
- Do not share personal items that can have blood or body fluids on them, like toothbrushes and razor blades.
- Do not have any kind of sex without protection. Always practice safe sex by using a latex or polyurethane condom or other barrier method to lower the chance of sexual contact with semen, vaginal secretions or blood.

Medicines are sometimes prescribed for purposes other than those listed in a Medication Guide. Do not use stavudine capsules for a condition for which it was not prescribed. Do not give stavudine capsules to other people, even if they have the same symptoms as you have. It may harm them. Do not keep medicine that is out of date or that you no longer need. Dispose of unused medicines through community take-back disposal programs when available or place stavudine capsules in an unrecognizable closed container in the household trash.

This Medication Guide summarizes the most important information about stavudine capsules. If you would like more information, talk with your healthcare provider. You can ask your healthcare provider or pharmacist for information about stavudine capsules that is written for health professionals. For more information, go to www.mylan.com or call Mylan Pharmaceuticals Inc. toll free at 1-877-446-3679 (1-877-4-INFO-RX).

What are the ingredients in stavudine capsules, USP?

Active Ingredient: stavudine, USP

Inactive Ingredients: lactose anhydrous, magnesium stearate, microcrystalline cellulose and sodium starch glycolate. The empty hard shell gelatin capsules contain gelatin and titanium dioxide. In addition, the 15 mg empty capsules contain D&C Red No. 28, D&C Yellow No. 10, FD&C Blue No. 1, FD&C Red No. 40, FD&C Yellow No. 6; the 20 mg empty capsules contain D&C Red No. 28, FD&C Blue No. 1, FD&C Red No. 40; the 30 mg empty capsules contain D&C Red No. 28, D&C Yellow No. 10, FD&C Red No. 40, FD&C Yellow No. 6; and the 40 mg empty capsules contain D&C Red No. 28, D&C Yellow No. 10, FD&C Yellow No. 6. The imprinting ink contains black iron oxide, potassium hydroxide, propylene glycol and shellac.

† The brand names mentioned are registered trademarks of their respective manufacturers.

This Medication Guide has been approved by the U.S. Food and Drug Administration.

Manufactured in India by:
Mylan Laboratories Limited
Hyderabad — 500 034, India
Code No.: MH/DRUGS/25/NKD/89

Manufactured for:
Mylan Pharmaceuticals Inc.
Morgantown, WV 26505 U.S.A.

This Product was Repackaged By:

State of Florida DOH Central Pharmacy
104-2 Hamilton Park Drive
Tallahassee, FL 32304
United States

PACKAGE LABEL

Label Image for 53808-0852
20mg